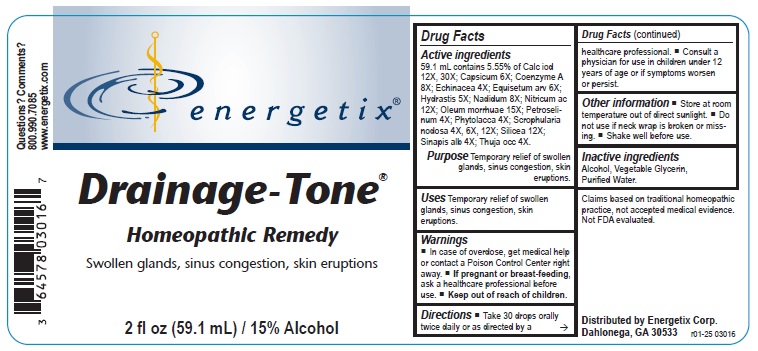 DRUG LABEL: Drainage-Tone
NDC: 64578-0142 | Form: LIQUID
Manufacturer: Energetix Corporation
Category: homeopathic | Type: HUMAN OTC DRUG LABEL
Date: 20250715

ACTIVE INGREDIENTS: CALCIUM IODIDE 12 [hp_X]/59.1 mL; CAPSICUM 6 [hp_X]/59.1 mL; COENZYME A 8 [hp_X]/59.1 mL; ECHINACEA ANGUSTIFOLIA 4 [hp_X]/59.1 mL; EQUISETUM ARVENSE TOP 6 [hp_X]/59.1 mL; GOLDENSEAL 5 [hp_X]/59.1 mL; NADIDE 8 [hp_X]/59.1 mL; NITRIC ACID 12 [hp_X]/59.1 mL; COD LIVER OIL 15 [hp_X]/59.1 mL; PETROSELINUM CRISPUM 4 [hp_X]/59.1 mL; PHYTOLACCA AMERICANA ROOT 4 [hp_X]/59.1 mL; SCROPHULARIA NODOSA 4 [hp_X]/59.1 mL; SILICON DIOXIDE 12 [hp_X]/59.1 mL; WHITE MUSTARD SEED 4 [hp_X]/59.1 mL; THUJA OCCIDENTALIS LEAFY TWIG 4 [hp_X]/59.1 mL
INACTIVE INGREDIENTS: WATER; ALCOHOL; GLYCERIN

Drainage-Tone

ACTIVE INGREDIENT

Active ingredients59.1 mL contains 5.55% of Calc iod 12X, 30X; Capsicum 6X; Coenzyme A 8X, Echinacea 4X; Equisetum arv 6X; Hydrastis 5X; Nadidum 8X; Nitricum ac 12X; Oleum morrhuae 15X; Petroselinum 4X; Phytolacca 4X; Scrophularia nodosa 4X, 6X, 12X; Silicea 12X; Sinapis alb 4X; Thuja occ 4X.

Claims based on traditional homeopathic practice, not accepted medical evidence. Not FDA evaluated.

Uses

Temporary relief of swollen glands, sinus congestion, skin eruptions.

Warnings

- In case of overdose, get medical help or contact a Poison Control Center right away.
- If pregnant or breast feeding,ask a health professional before use.

• Keep out of reach of children.

Directions

- Take 30 drops orally twice daily or as directed by a healthcare professional.
- Consult a physician for use in children under 12 years or age or if symptoms worsen or persist.

Other information

- Store at room temperature out of direct sunlight.
- Do not use if neck wrap is broken or missing.
- Shake well before use.

Inactive ingredients

Alcohol, Vegetable Glycerin, Purified Water.

QUESTIONS

Distributed by Energetix Corp.

Dahlonega, GA 30533

Questions? Comments?

800.990.7085

www.energetix.com

PACKAGE LABEL

energetix

Drainage-Tone

Homeopathic Remedy

Swollen glands, sinus congestion, skin eruptions

2 fl oz (59.1 mL) / 15% Alcohol

PURPOSE

Purpose Temporary relief of swollen glands, sinus congestion, skin eruptions.